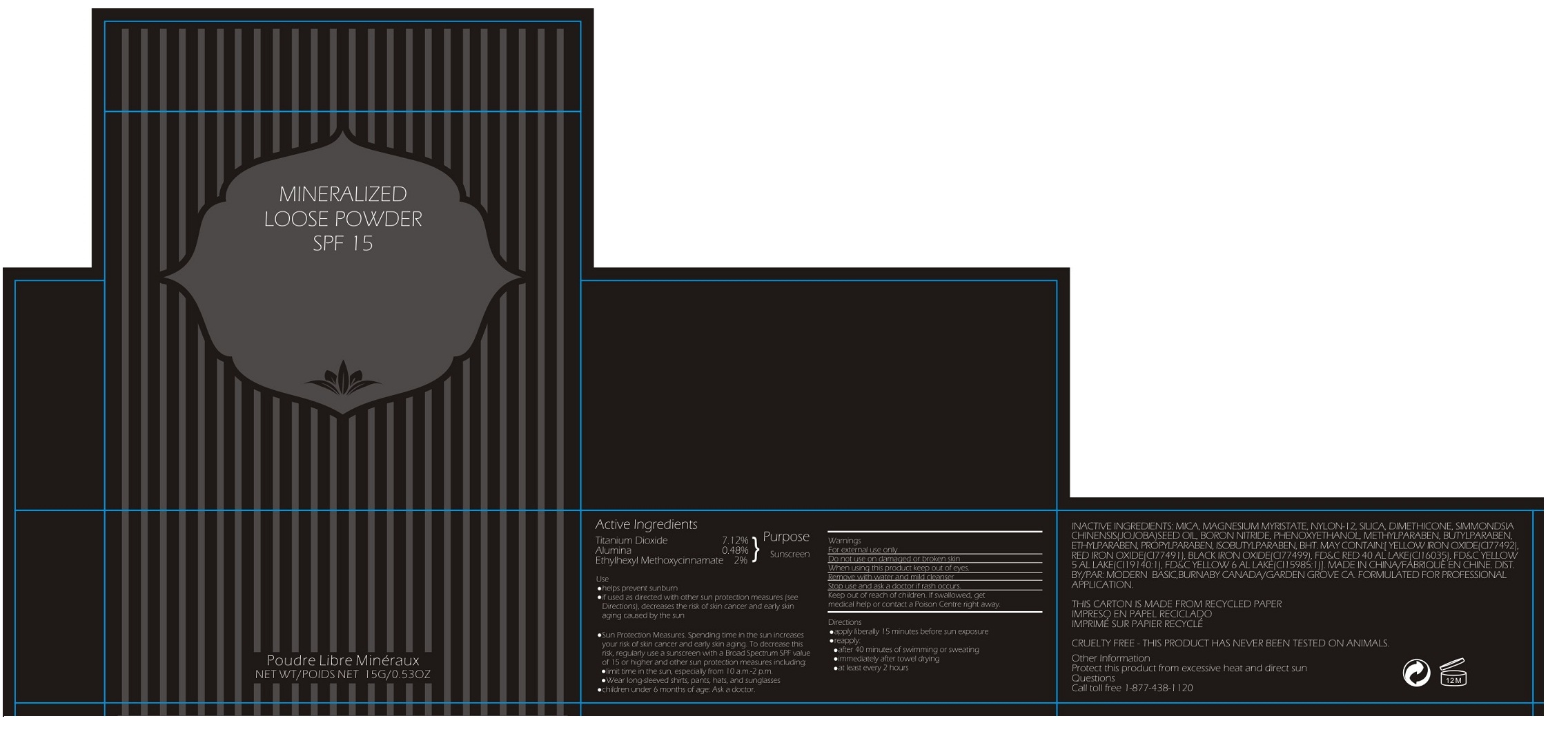 DRUG LABEL: Mineralized Loose Powder SPF 15
NDC: 69349-102 | Form: POWDER
Manufacturer: Modern Beauty Limited
Category: otc | Type: HUMAN OTC DRUG LABEL
Date: 20151205

ACTIVE INGREDIENTS: TITANIUM DIOXIDE 7.12 mg/1 g; OCTINOXATE 2 mg/1 g
INACTIVE INGREDIENTS: MICA; MAGNESIUM MYRISTATE; NYLON-12; SILICON DIOXIDE; DIMETHICONE; JOJOBA OIL; BORON NITRIDE; PHENOXYETHANOL; METHYLPARABEN; BUTYLPARABEN; ETHYLPARABEN; PROPYLPARABEN; ISOBUTYLPARABEN; BUTYLATED HYDROXYTOLUENE; FERRIC OXIDE YELLOW; FERRIC OXIDE RED; FERROSOFERRIC OXIDE; FD&C RED NO. 40; FD&C YELLOW NO. 5; FD&C YELLOW NO. 6

MINERALIZED LOOSE POWDER SPF 15

Active Ingredients

Titanium Dioxide 7.12%

Ethylhexyl Methoxycinnamate 2%

Purpose

Sunscreen

Keep out of reach of children. If swallowed, get medical help or contact Poison Centre right away.

Use

•helps prevent sunburn
•if used as directed with other sun protection measures (see Directions), decreases the risk of skin cancer and early skin aging caused by the sun

Warnings

For external use only

Do not use on damaged or broken skin

When using this product keep out of eyes.

Remove with water and mild cleanser

Stop use and ask a doctor if rash occurs.

Directions

•apply liberally 15 minutes before sun exposure
•reapply:
•after 40 minutes of swimming or sweating
•immediately after towel drying
•at least every 2 hours
•Sun Protection Measures. Spending time in the sun increases your risk of skin cancer and early skin aging. To decrease this risk, regularly use a sunscreen with a Broad Spectrum SPF value of 15 or higher and other sun protection measures including:
•limit time in the sun, especially from 10 a.m-2 p.m
•Wear long-sleeved shirts, pants, hats and sunglasses
•children under 6 months of age: Ask a doctor.

INACTIVE INGREDIENT

INACTIVE INGREDIENTS: MICA, MAGNESIUM MYRISTATE, NYLON-12, SILICA, DIMETHICONE, SIMMONDSIA CHINENSIS(JOJOBA)SEED OIL, BORON NITRIDE, PHENOXYETHANOL, METHYLPARABEN, BUTYLPARABEN, ETHYLPARABEN, PROPYLPARABEN, ISOBUTYLPARABEN, BHT, MAY CONTAIN:[YELLOW IRON OXIDE(CI77492), RED IRON OXIDE(CI77491), BLACK IRON OXIDE(CI77499), FD&C RED 40 AL LAKE(CI16035), FD&C YELLOW 5 AL LAKE(CI19140:1), FD&C YELLOW 6 AL LAKE(CI15985:1)]

Other Information

Protect this product from excessive heat and direct sun

Questions

Call toll free 1-877-438-1120

FORMULATED FOR PROFESSIONAL APPLICATION

THIS CARTON IS MADE FROM RECYCLED PAPER

CRUELTY FREE - THIS PRODUCT HAS NEVER BEEN TESTED ON ANIMALS.

MADE IN CHINA

MODERN BASIC,BURNABY CANADA/GARDEN GROVE CA.